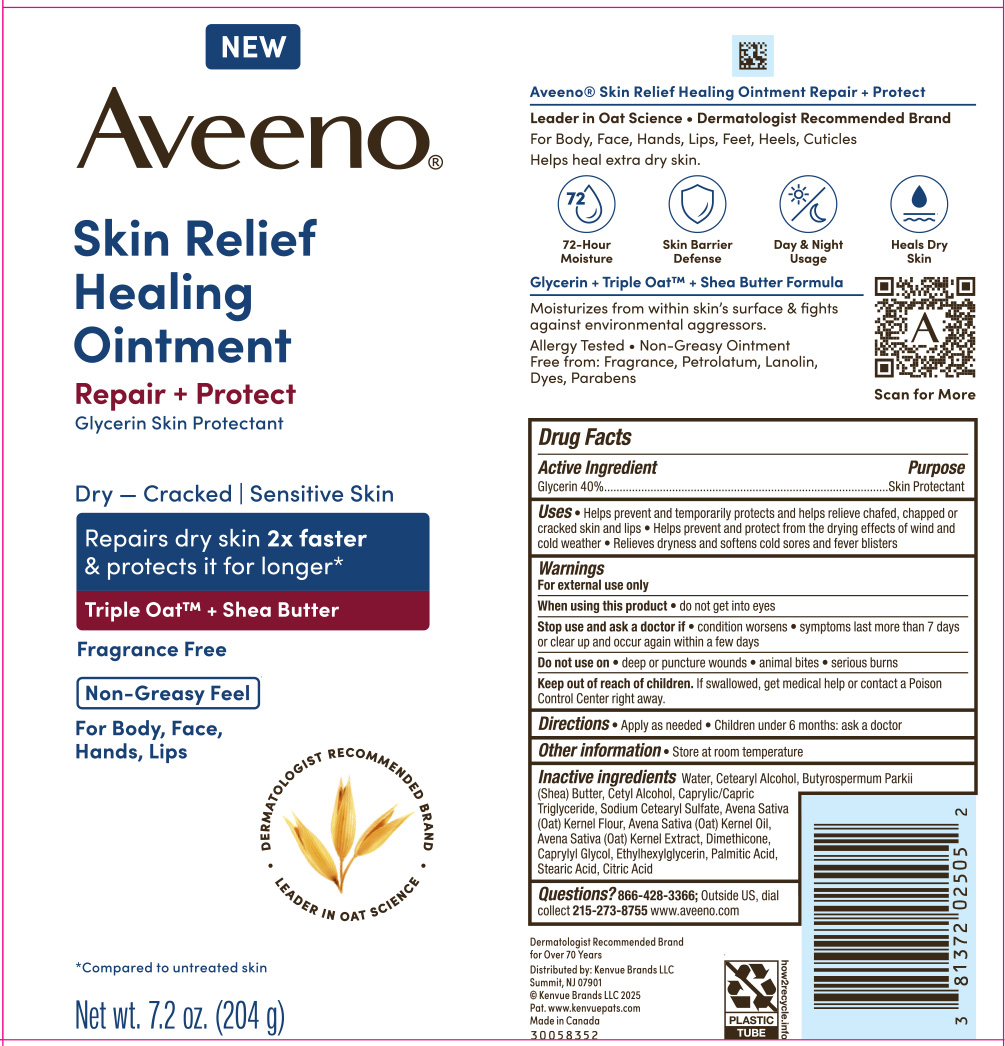 DRUG LABEL: Aveeno Skin Relief Healing
NDC: 69968-0929 | Form: OINTMENT
Manufacturer: Kenvue Brands LLC
Category: otc | Type: HUMAN OTC DRUG LABEL
Date: 20250505

ACTIVE INGREDIENTS: GLYCERIN 400 mg/1 g
INACTIVE INGREDIENTS: STEARIC ACID; WATER; CETEARYL ALCOHOL; BUTYROSPERMUM PARKII (SHEA) BUTTER; CETYL ALCOHOL; CAPRYLIC/CAPRIC TRIGLYCERIDE; SODIUM CETEARYL SULFATE; OATMEAL; OAT; DIMETHICONE; CAPRYLYL GLYCOL; ETHYLHEXYLGLYCERIN; PALMITIC ACID; CITRIC ACID; AVENA SATIVA (OAT) KERNEL OIL

Aveeno Skin Relief Healing Ointment

Drug Facts

Active ingredient

Glycerin 40%

Purpose

Skin Protectant

Uses

- Helps prevent and temporarily protects and help relieve chafed, chapped or cracked skin and lips
- Helps prevent and protect from the drying effects of wind and cold weather
- Relieves dryness and softens cold sores and fever blisters

Warnings

For external use only

When using this product

do not get into eyes

Stop use and ask a doctor if

- condition worsens
- symptoms last more than 7 days or clear up and occur again within a few days

Do not use on

- deep or puncture wounds
- animal bites
- serious burns

Keep out of reach of children. If swallowed, get medical help or contact a Poison Control Center right away.

Directions

- Apply as needed.
- Children under 6 months: ask a doctor

Other information

Store at room temperature

Inactive ingredients

Water, Cetearyl Alcohol, Butyrospermum Parkii (Shea) Butter, Cetyl Alcohol, Caprylic/Capric Triglyceride, Sodium Cetearyl Sulfate, Avena Sativa (Oat) Kernel Flour, Avena Sativa (Oat) Kernel Oil, Avena Sativa (Oat) Kernel Extract, Dimethicone, Caprylyl Glycol, Ethylhexylglycerin, Palmitic Acid, Stearic Acid, Citric Acid

Questions?

866-428-3366; Outside US, dial collect 215-273-8755 www.aveeno.com

Distributed by: Kenvue Brands LLC
Skillman, NJ 07901

PRINCIPAL DISPLAY PANEL - 204 g Tube Label

NEW

Aveeno®

Skin Relief

Healing

Ointment

Repair + Protect

Glycerin Skin Protectant

Dry – Cracked | Sensitive Skin

Repairs dry skin 2x faster

& protects it for longer*

Triple Oat™ + Shea Butter

Fragrance Free

Non-Greasy Feel

For Body, Face,

Hands, Lips

DERMATOLOGIST RECOMMENDED BRAND

LEADER IN OAT SCIENCE

*Compared to untreated skin

Net wt. 7.2 oz. (204 g)